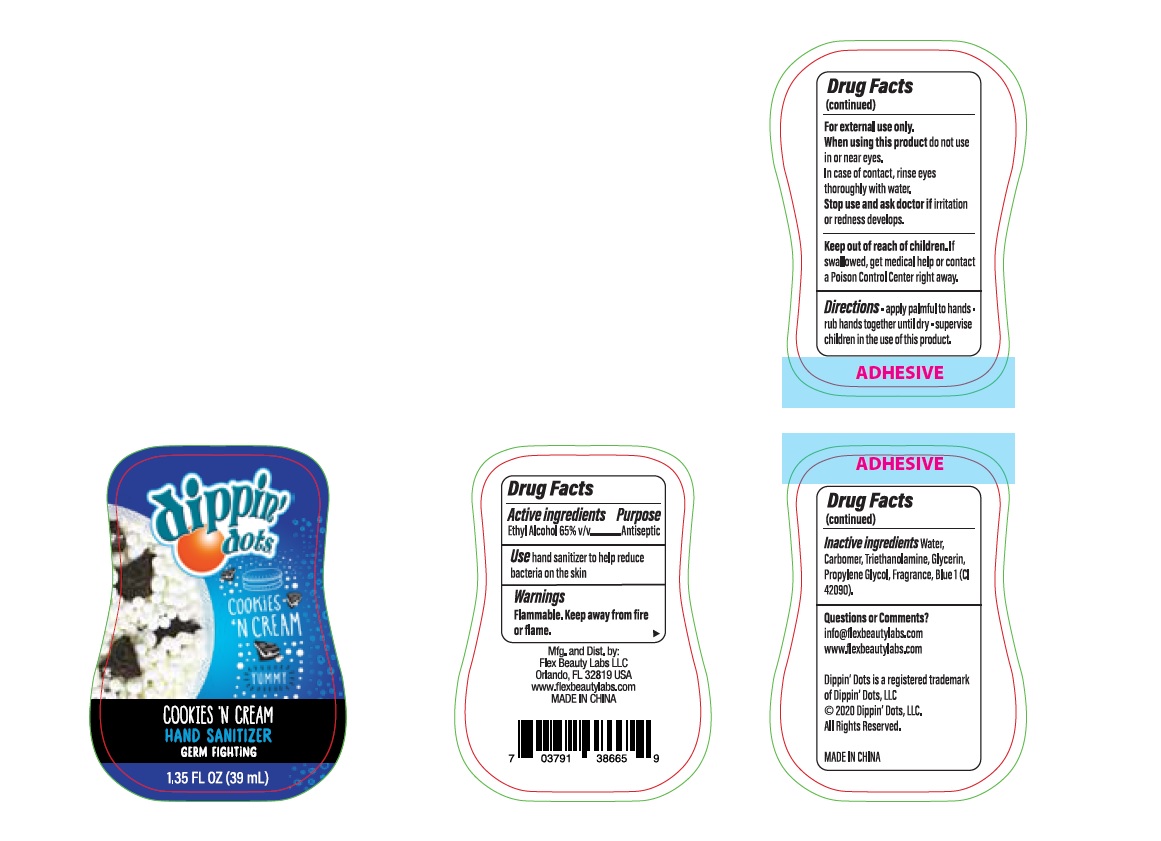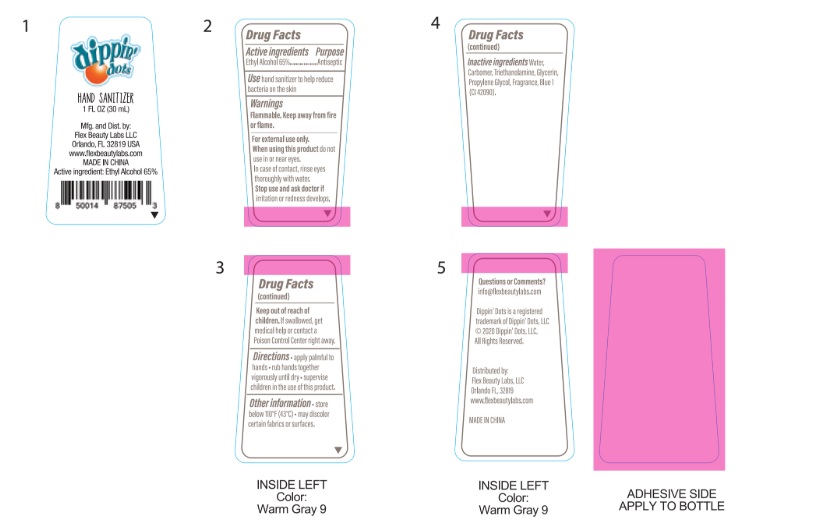 DRUG LABEL: Dippin Dots Hand Sanitizer
NDC: 72308-005 | Form: GEL
Manufacturer: Flex Beauty Labs
Category: otc | Type: HUMAN OTC DRUG LABEL
Date: 20200818

ACTIVE INGREDIENTS: ALCOHOL 0.65 mL/1 mL
INACTIVE INGREDIENTS: WATER; TROLAMINE; CARBOMER COPOLYMER TYPE B (ALLYL PENTAERYTHRITOL CROSSLINKED); PROPYLENE GLYCOL; GLYCERIN; FD&C BLUE NO. 1

Dippin Dots Hand Sanitizer

Active Ingredients

Ethyl Alcohol 65%.................Antiseptic

Purpose

Antiseptic

Use

hand sanitizer to help reduce bacteria on the skin

Safety Instructions

Flammable, Keep away from fire and flame

When using this product

In case of contact,rinse eyes thoroughly with water

Do not use in or near eyes.

KEEP OUT OF REACH OF CHILDREN

If swallowed, get medical help or contact Poison Control center right away.

Other Information

Store below 110°F (43°C)
May discolor certain fabrics or surfaces.

Inactive Ingredients

Water (aqua), Triethanolamine, Carbomer, Fragrance, Glycerin. Propylene Glycol,Blue 1

Directions

- apply palmful to hands.
- rub hands together vigorously until dry.
- supervise children in the use of this product.